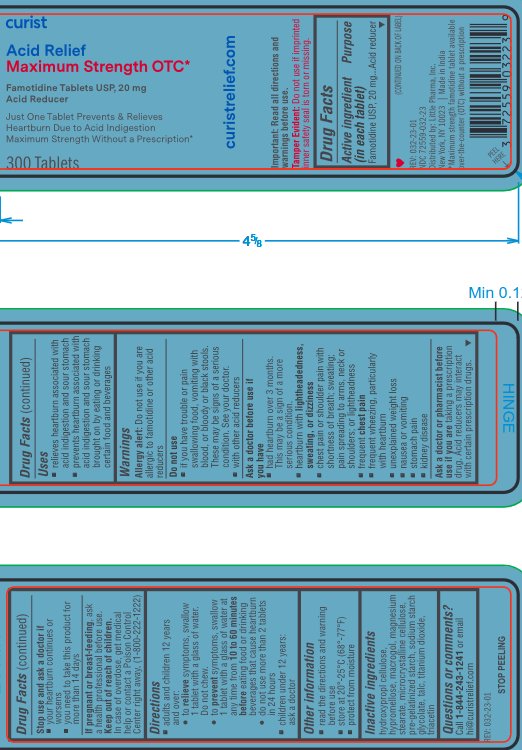 DRUG LABEL: Curist Acid Relief
NDC: 72559-032 | Form: TABLET
Manufacturer: Little Pharma, Inc.
Category: otc | Type: HUMAN OTC DRUG LABEL
Date: 20240126

ACTIVE INGREDIENTS: FAMOTIDINE 20 mg/1 1
INACTIVE INGREDIENTS: HYPROMELLOSE 2910 (6 MPA.S); TALC; TITANIUM DIOXIDE; SODIUM STARCH GLYCOLATE TYPE A; MAGNESIUM STEARATE; TRIACETIN; POLYETHYLENE GLYCOL 4000; MICROCRYSTALLINE CELLULOSE; HYDROXYPROPYL CELLULOSE (110000 WAMW); STARCH, CORN

Curist Acid Relief (famotidine 20 mg tablets)

curistrelief.com

Important: Read all directions and warnings before use.

Tamper Evident: do not use if imprinted inner safety seal is torn or missing

Drug Facts

Active ingredient (in each tablet)

Famotidine USP, 20 mg

Purpose

Acid reducer

(CONTINUED ON BACK OF LABEL)

REV: 032-23-01

NDC 72559-032-23

Distributed by: Little Pharma, Inc.

New York, NY 10023 | Made in India

*Maximum strength famotidine tablet available over-the-counter (OTC) without a prescription

PEEL HERE

Uses

- relieves heartburn associated with acid indigestion and sour stomach
- prevents heartburn associated with acid indigestion and sour stomach brought on by eating or drinking certain food and beverages

Warnings

Allergy alert: Do not use if you are allergic to famotidine or other acid reducers

Do not use

- if you have trouble or pain swallowing food, vomiting with blood, or bloody or black stools. These may be signs of a serious condition. See your doctor.
- with other acid reducers

Ask a doctor before use if you have

- had heartburn over 3 months. This may be a sign of a more serious condition.
- heartburn with lighheadedness, sweating, or dizziness
- chest pain or shoulder pain with shortness of breath; sweating; pain spreading to arms, neck or shoulders; or lightheadness
- frequent chest pain
- frequent wheezing, particularly with heartburn
- unexplained weight loss
- nausea or vomiting
- stomach pain
- kidney disease

Ask a doctor or pharmacist before use if you are taking a prescription drug. Acid reducers may interact with certain prescription drugs.

Stop use and ask a doctor if

- your heartburn continues or worsens
- you need to take this product for more than 14 days

PREGNANCY OR BREAST FEEDING

If pregnant or breast-feeding, ask a health professional before use.

Keep out of reach of children.

In case of overdose, get medical help or contact a Poison Control Center right away. (1-800-222-1222)

DOSAGE AND ADMINISTRATION

- adults and children 12 years and over:
- to relieve symptoms, swallow 1 tablet with a glass of water. Do not chew.
- to prevent symptoms, swallow 1 tablet with a glass of water at any time from 10 to 60 minutes before eating food or drinking beverages that cause heartburn
- do not use more than 2 tablets in 24 hours
- children under 12 years: ask a doctor

Other information

- read the directions and warning before use
- store at 20°-25°C (68°-77°F)
- protect from moisture

INACTIVE INGREDIENT

hydroxypropyl cellulose, hypromellose, macrogol, magnesium stearate, microcrystalline cellulose, pre-gelatinized starch, sodium starch glycolate, talc, titanium dioxide, triacetin

Questions or comments?

Call 1-844-243-1241 or email hi@curistrelief.com

REV: 032-23-01

STOP PEELING

PACKAGE LABEL

curist

Acid Relief

Maximum Strength OTC*

Famotidine Tablets USP, 20 mg

Acid Reducer

Just One Tablet Prevents & Relieves Heartburn Due to Acid Indigestion

Maximum Strength Without a Prescription*

300 Tablets